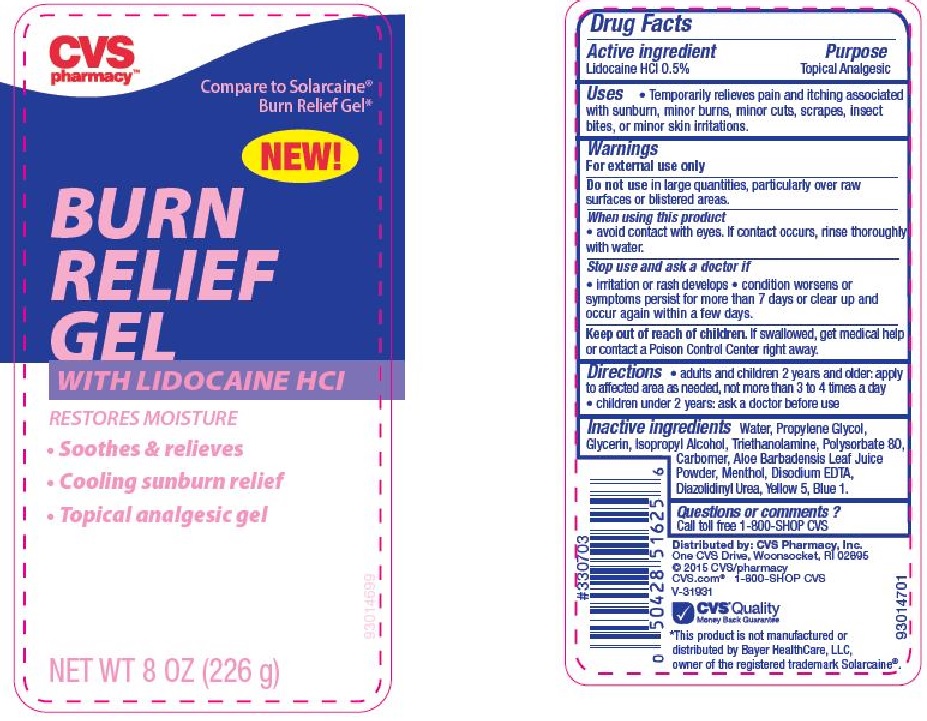 DRUG LABEL: CVS Burn Relief w/Lido 8oz
NDC: 59779-670 | Form: GEL
Manufacturer: CVS Pharmacy
Category: otc | Type: HUMAN OTC DRUG LABEL
Date: 20160323

ACTIVE INGREDIENTS: LIDOCAINE HYDROCHLORIDE 0.5 g/100 g
INACTIVE INGREDIENTS: WATER; PROPYLENE GLYCOL; GLYCERIN; ISOPROPYL ALCOHOL; TROLAMINE; POLYSORBATE 80; ALOE VERA LEAF; MENTHOL, UNSPECIFIED FORM; EDETATE DISODIUM; DIAZOLIDINYL UREA; FD&C YELLOW NO. 5; FD&C BLUE NO. 1

Drug Facts

Active ingredient

Lidocaine HCl 0.5%

Purpose

Topical Analgesic

Uses

- Temporarily relieves pain and itching associated with sunburn, minor burns, minor cuts, scrapes, insect bites, or minor skin irritations.

Warnings

For external use only

Do not use

in large quantities, particularly over raw surfaces or blistered areas.

When using this product

- avoid contact with eyes. If contact occurs, rinse thoroughly with water.

Stop use and ask a doctor if

- irritation or rash develops
- condition worsens or symptoms persist for more than 7 days or clear up and occur again within a few days.

Keep out of reach of children.

If swallowed, get medical help or contact a Poison Control Center right away.

Directions

- adults and children 2 years and older:apply to affected areas as needed, not more than 3 to 4 times a day
- children under 2 years:ask a doctor before use

Inactive ingredients

Water, Propylene Glycol, Glycerin, Isopropyl Alcohol, Triethanolamine, Polysorbate 80, Carbomer, Aloe Barbadensis Leaf Juice Powder, Menthol, Disodium EDTA, Diazolidinyl Urea, Yellow 5, Blue 1.

Questions or comments?

Call toll free 1-800-SHOP CVS

Principal Display Panel

CVS pharmacy

Compare to Solarcaine

Burn Relief Gel

NEW!

BURN RELIEF GEL

WITH LIDOCAINE HCl

RESTORES MOISTURE

- Soothes and relieves

- Cooling sunburn relief

- Topical analgesic gel

NET WT 8 OZ (226 g)